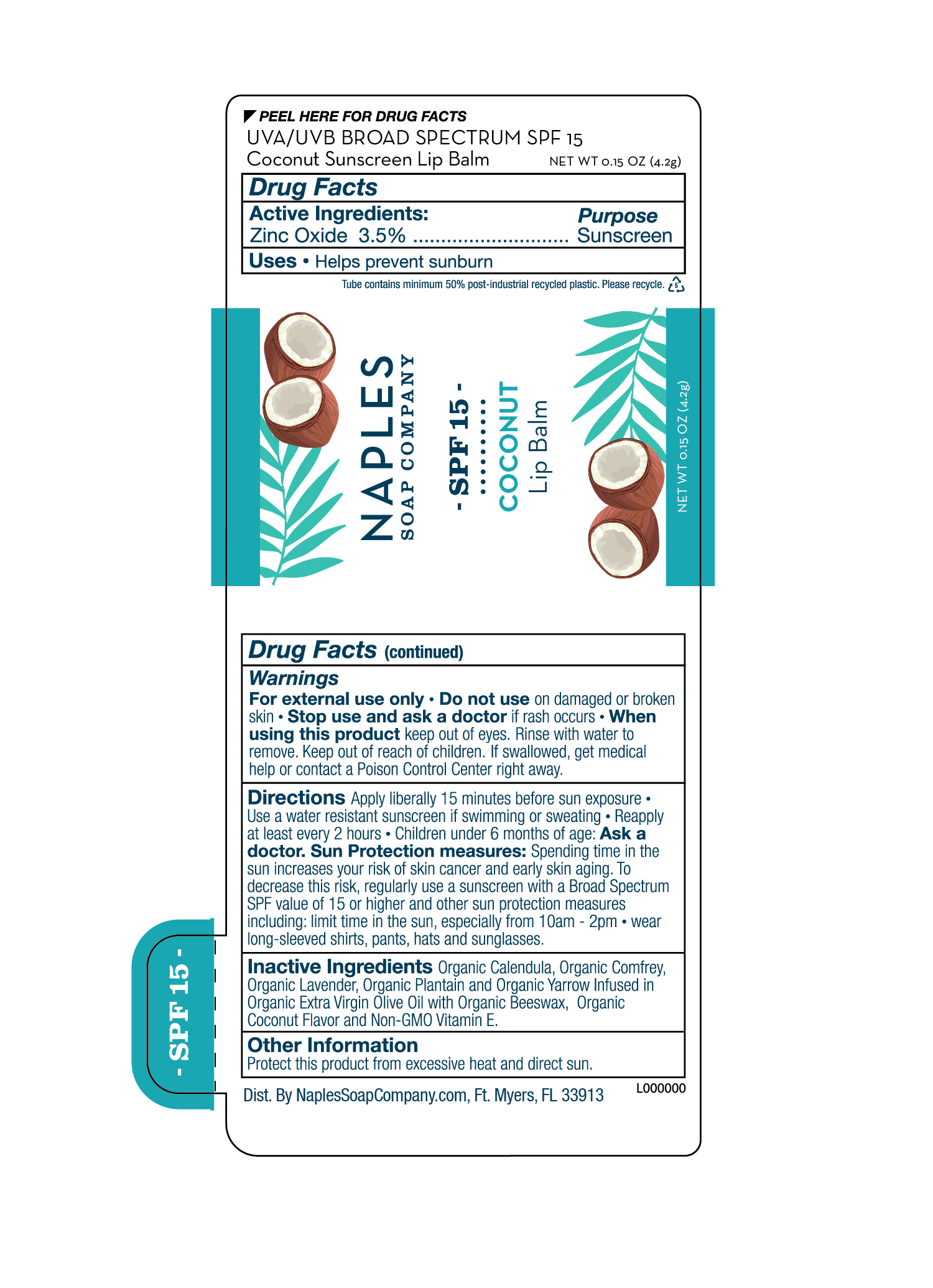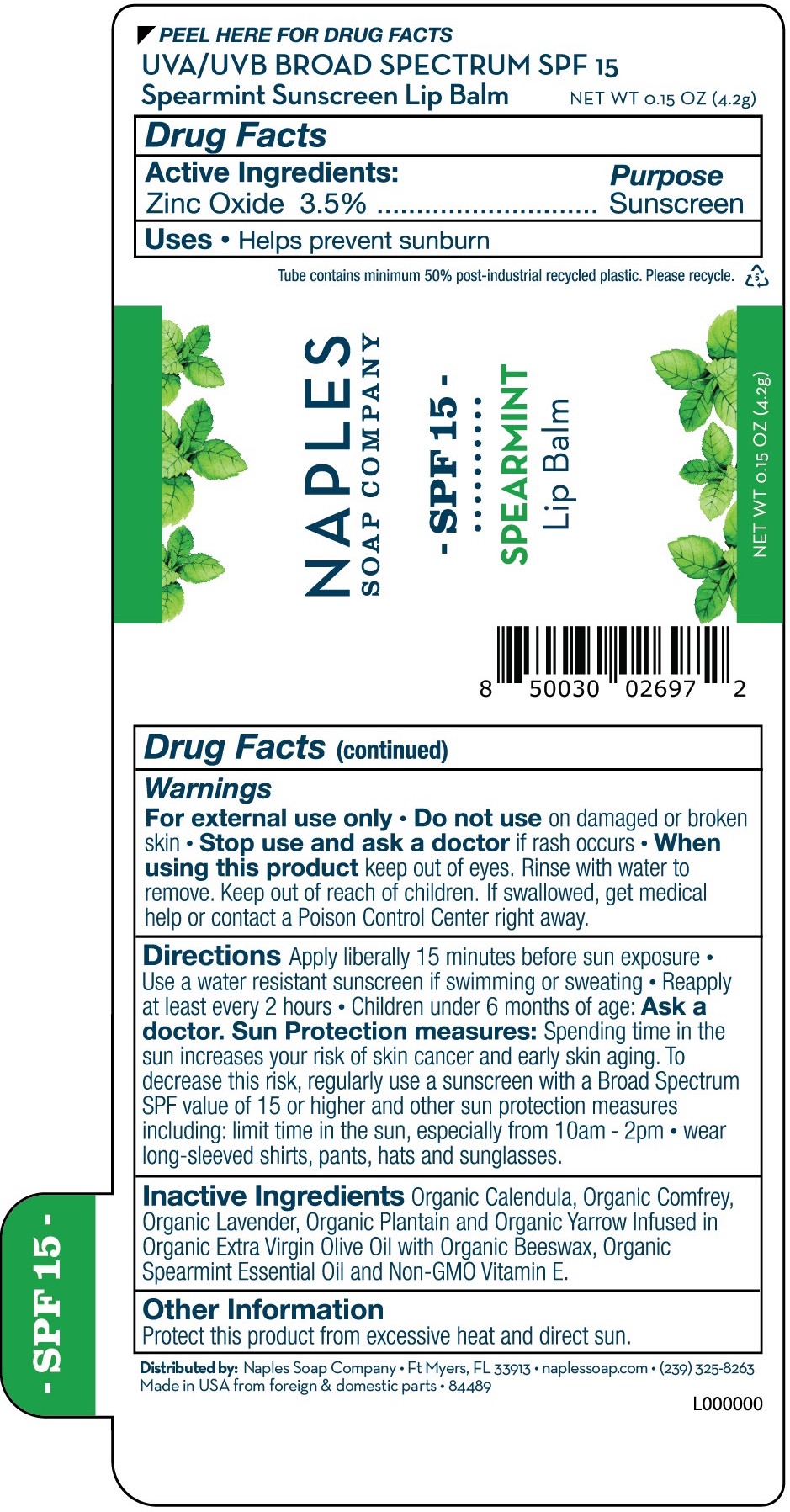 DRUG LABEL: SPF 15 Spearmint Lip Balm
NDC: 84489-269 | Form: STICK
Manufacturer: Naples Soap Company, Inc.
Category: otc | Type: HUMAN OTC DRUG LABEL
Date: 20241029

ACTIVE INGREDIENTS: ZINC OXIDE 35 mg/1 g
INACTIVE INGREDIENTS: YELLOW WAX; LAVANDULA ANGUSTIFOLIA FLOWER; OLIVE OIL; TOCOPHEROL; PLANTAGO MAJOR LEAF; ACHILLEA MILLEFOLIUM FLOWER; SPEARMINT OIL; CALENDULA OFFICINALIS FLOWER; COMFREY LEAF

UVA/UVB BROAD SPECTRUM SPF 15

Spearmint Sunscreen Lip Balm

Coconut Sunscreen Lip Balm

Active ingredient

Zinc Oxide 3.5%

Purpose

Sunscreen

Uses

- Helps prevent sunburn

Warnings

For external use only

- Do not use on damaged or broken skin

- Stop use and ask a doctor if rash occurs

- When using this product keep out of eyes. Rinse with water to remove.

Keep out of reach of children. If swallowed, get medical help or contact a Poison Control Center right away.

Directions

- Apply liberally 15 minutes before sun exposure
- Use a water resistant sunscreen if swimming or sweating
- Reapply at least every 2 hours
- Children under 6 months of age: Ask a doctor

Sun Protection measures: Spending time in the sun increases your risk of skin cancer and early skin aging. To decrease this risk, regularly use a sunscreen with a Broad Spectrum SPF value of 15 or higher and other sun protection measures including:

- limit time in the sun, especially from 10 a.m. - 2 p.m.
- wear long-sleeved shirts, pants, hats and sunglasses

Other information

- Protect this product from excessive heat and direct sun

Inactive ingredients

Organic Calendula, Organic Comfrey, Organic Lavender, Organic Plantain and Organic Yarrow Infused in Organic Extra Virgin Olive Oil with Organic Beeswax, Organic Coconut Flavor and Non-GMO Vitamin E.

PACKAGE LABEL

NAPLES SOAP COMPANY

SPF 15

Spearmint Lip Balm

NET WT 0.15 OZ (4.2 g)

PACKAGE LABEL

NAPLES SOAP COMPANY

SPF 15

Coconut Lip Balm

NET WT 0.15 OZ (4.2 g)